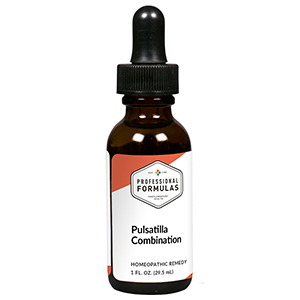 DRUG LABEL: Pulsatilla Combination
NDC: 63083-9238 | Form: LIQUID
Manufacturer: Professional Complementary Health Formulas
Category: homeopathic | Type: HUMAN OTC DRUG LABEL
Date: 20190815

ACTIVE INGREDIENTS: BRYONIA ALBA ROOT 4 [hp_X]/29.5 mL; LYCOPODIUM CLAVATUM SPORE 4 [hp_X]/29.5 mL; STRYCHNOS NUX-VOMICA SEED 4 [hp_X]/29.5 mL; PULSATILLA MONTANA WHOLE 4 [hp_X]/29.5 mL; SILVER NITRATE 6 [hp_X]/29.5 mL; CITRULLUS COLOCYNTHIS FRUIT PULP 6 [hp_X]/29.5 mL; ANTIMONY TRISULFIDE 8 [hp_X]/29.5 mL; ARSENIC TRIOXIDE 8 [hp_X]/29.5 mL; ACTIVATED CHARCOAL 8 [hp_X]/29.5 mL; BOS TAURUS COLON 12 [hp_X]/29.5 mL; GIARDIA LAMBLIA 12 [hp_X]/29.5 mL; BOS TAURUS LARGE INTESTINE 12 [hp_X]/29.5 mL; MERCURIC CHLORIDE 12 [hp_X]/29.5 mL; TRIPE 12 [hp_X]/29.5 mL
INACTIVE INGREDIENTS: ALCOHOL; WATER

R238

ACTIVE INGREDIENTS

Bryonia 4X
Lycopodium clavatum 4X
Nux vomica 4X
Pulsatilla 4X
Argentum nitricum 6X
Colocynthis 6X
Antimonium crudum 8X
Arsenicum album 8X
Carbo vegetabilis 8X
Colon 12X
Giardia lamblia 12X
Intestine 12X
Mercurius corrosivus 12X
Stomach 12X

QUESTIONS

Professional Formulas

PO Box 2034 Lake Oswego, OR 97035

INDICATIONS

For the temporary relief of heartburn, indigestion, or nausea.*

PURPOSE

*Claims based on traditional homeopathic practice, not accepted medical evidence. Not FDA evaluated.

WARNINGS

In case of overdose, get medical help or contact a poison control center right away.

Keep out of the reach of children.

PREGNANCY OR BREAST FEEDING

If pregnant or breastfeeding, ask a healthcare professional before use.

DIRECTIONS

Place drops under tongue 30 minutes before/after meals. Adults and children 12 years and over: Take 10 drops up to 3 times per day. Consult a physician for use in children under 12 years of age.

OTHER INFORMATION

Tamper resistant. If seal is broken, do not use. After opening, close container tightly and store at room temperature away from heat.

INACTIVE INGREDIENTS

40% ethanol, purified water.

LABEL

Est 1985

Professional Formulas

Complementary Health

Pulsatilla Combination

Homeopathic Remedy

1 FL. OZ. (29.5 mL)